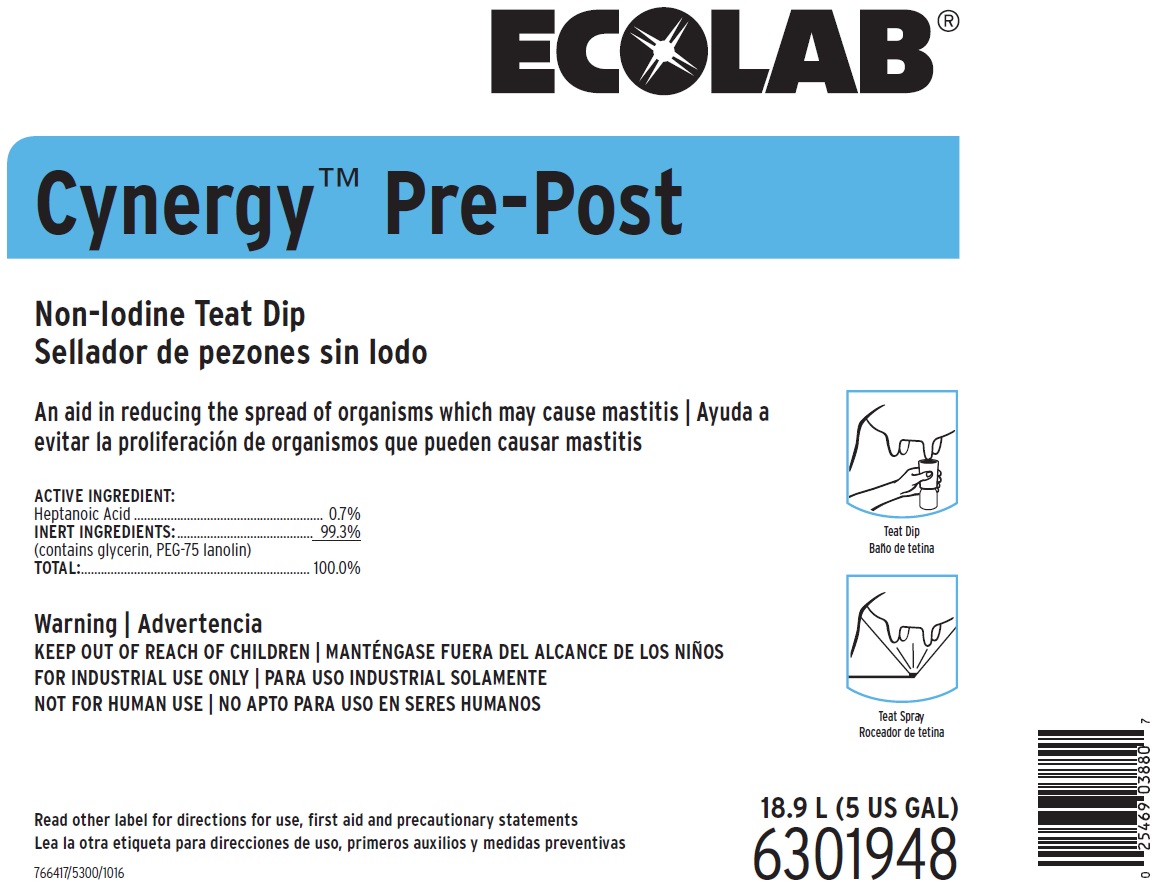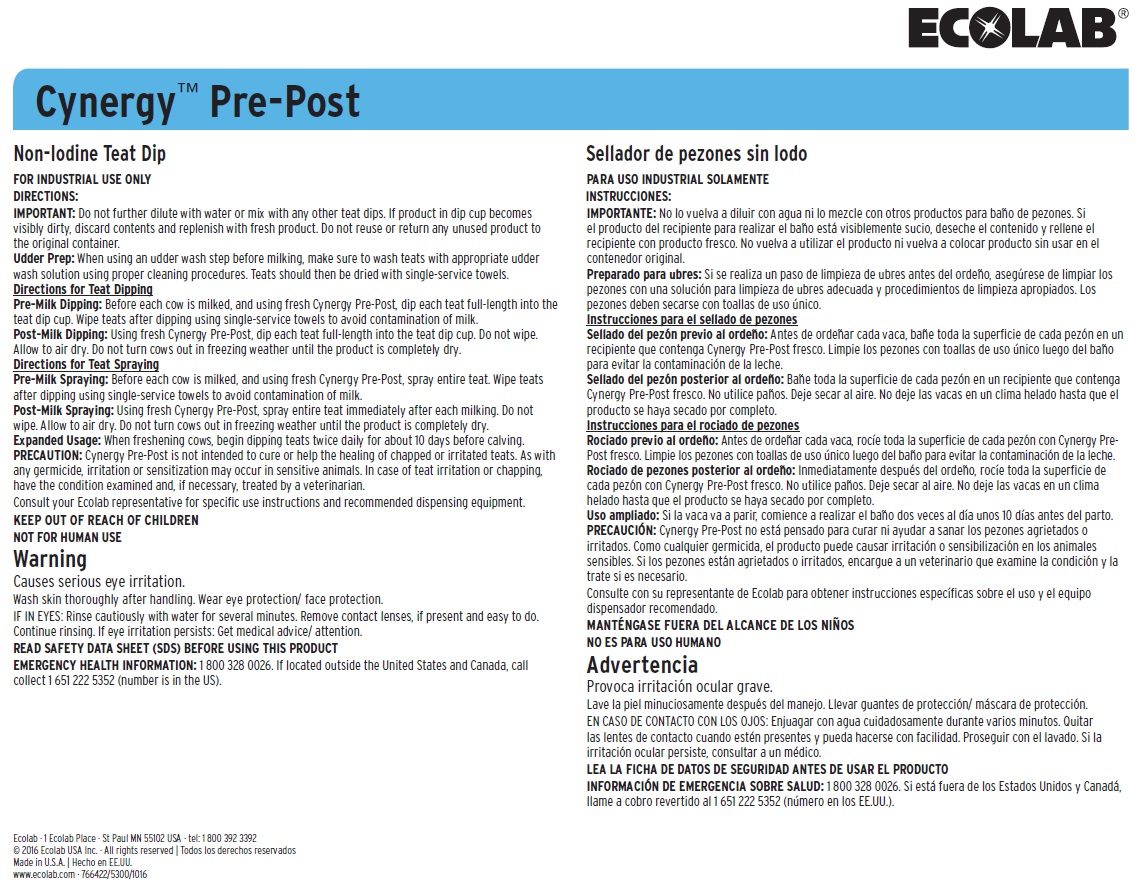 DRUG LABEL: Cynergy Pre-Post
NDC: 47593-447 | Form: SOLUTION
Manufacturer: Ecolab Inc.
Category: animal | Type: OTC ANIMAL DRUG LABEL
Date: 20250826

ACTIVE INGREDIENTS: HEPTANOIC ACID 7 mg/1 mL
INACTIVE INGREDIENTS: WATER; GLYCERIN; PEG-75 LANOLIN

KEEP OUT OF REACH OF CHILDREN

FOR INDUSTRIAL USE ONLY

NOT FOR HUMAN USE

Warning

Causes serious eye irritation.

Wash skin thoroughly after handling. Wear eye protection/ face protection.

IF IN EYES: Rinse cautiously with water for several minutes. Remove contact lenses, if present and easy to do. Continue rinsing. If eye irritation persists: Get medical advice/ attention

DIRECTIONS:

IMPORTANT: Do not further dilute with water or mix with any other teat dips. If product in dip cup becomes visibly dirty, discard contents and replenish with fresh product. Do not reuse or return any unused product to the original container.

Udder Prep: When using an udder wash step before milking, make sure to wash teats with appropriate udder wash solution using proper cleaning procedures. Teats should then be dried with single-service towels.

Directions for Teat Dipping

Pre-Milk Dipping: Before each cow is milked, and using fresh Cynergy Pre-Post, dip each teat full-length into the teat dip cup. Wipe teats after dipping using single-service towels to avoid contamination of milk.

Post-Milk Dipping: Using fresh Cynergy Pre-Post, dip each teat full-length into the teat dip cup. Do not wipe. Allow to air dry. Do not turn cows out in freezing weather until the product is completely dry.

Directions for Teat Spraying

Pre-Milk Spraying: Before each cow is milked, and using fresh Cynergy Pre-Post, spray entire teat. Wipe teats after dipping using single-service towels to avoid contamination of milk.

Post-Milk Spraying: Using fresh Cynergy Pre-Post, spray entire teat immediately after each milking. Do not wipe. Allow to air dry. Do not turn cows out in freezing weather until the product is completely dry. Expanded Usage: When freshening cows, begin dipping teats twice daily for about 10 days before calving.

PRECAUTION: Cynergy Pre-Post is not intended to cure or help the healing of chapped or irritated teats. As with any germicide, irritation or sensitization may occur in sensitive animals. In case of teat irritation or chapping, have the condition examined and, if necessary, treated by a veterinarian.

Consult your Ecolab representative for specific use instructions and recommended dispensing equipment.

OTHER SAFETY INFORMATION

READ SAFETY DATA SHEET (SDS) BEFORE USING THIS PRODUCT

EMERGENCY HEALTH INFORMATION: 1 800 328 0026. If located outside the United States and Canada, call collect 1 651 222 5352 (number is in the US).

PACKAGE LABEL

Ecolab®

Cynergy™ Pre-Post

Non-Iodine Teat Dip

An aid in reducing the spread of organisms which may cause mastitis

ACTIVE INGREDIENT:

Heptanoic Acid ...................................................... 0.7%

INERT INGREDIENTS: ......................................... 99.3%

(contains glycerin, PEG-75 lanolin)

TOTAL:............................................................... 100.0%

766417/5300/1016

Ecolab · 1 Ecolab Place · St Paul MN 55102 USA · tel: 1 800 392 3392

© 2016 Ecolab USA Inc. · All rights reserved

Made in U.S.A. www.ecolab.com · 766422/5300/1016